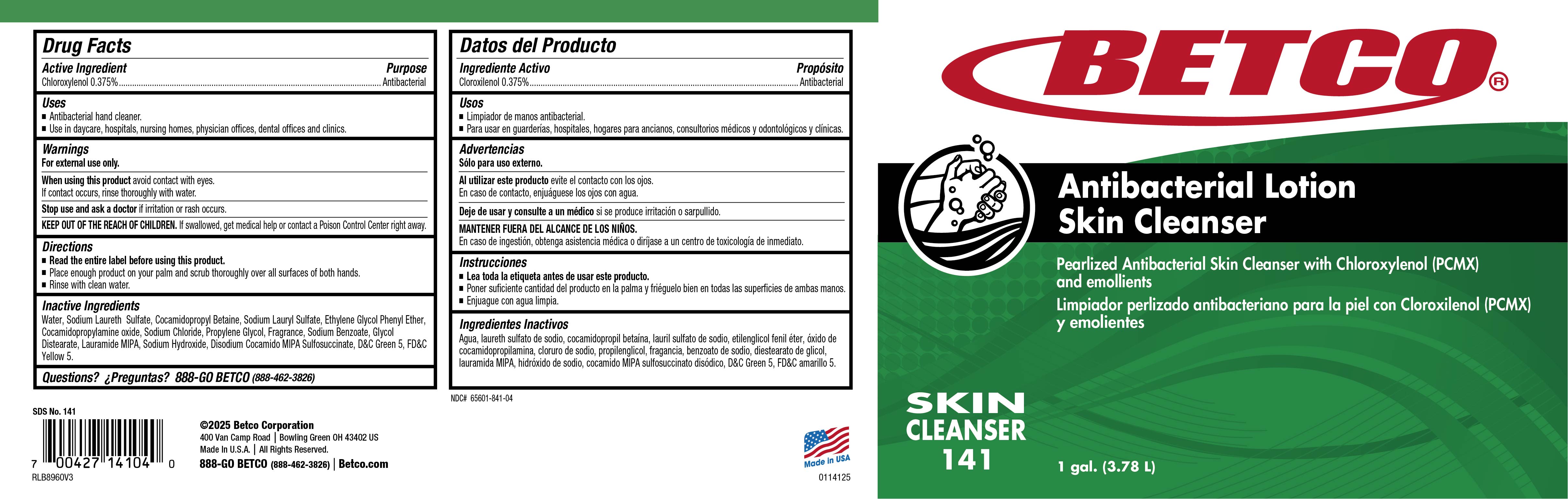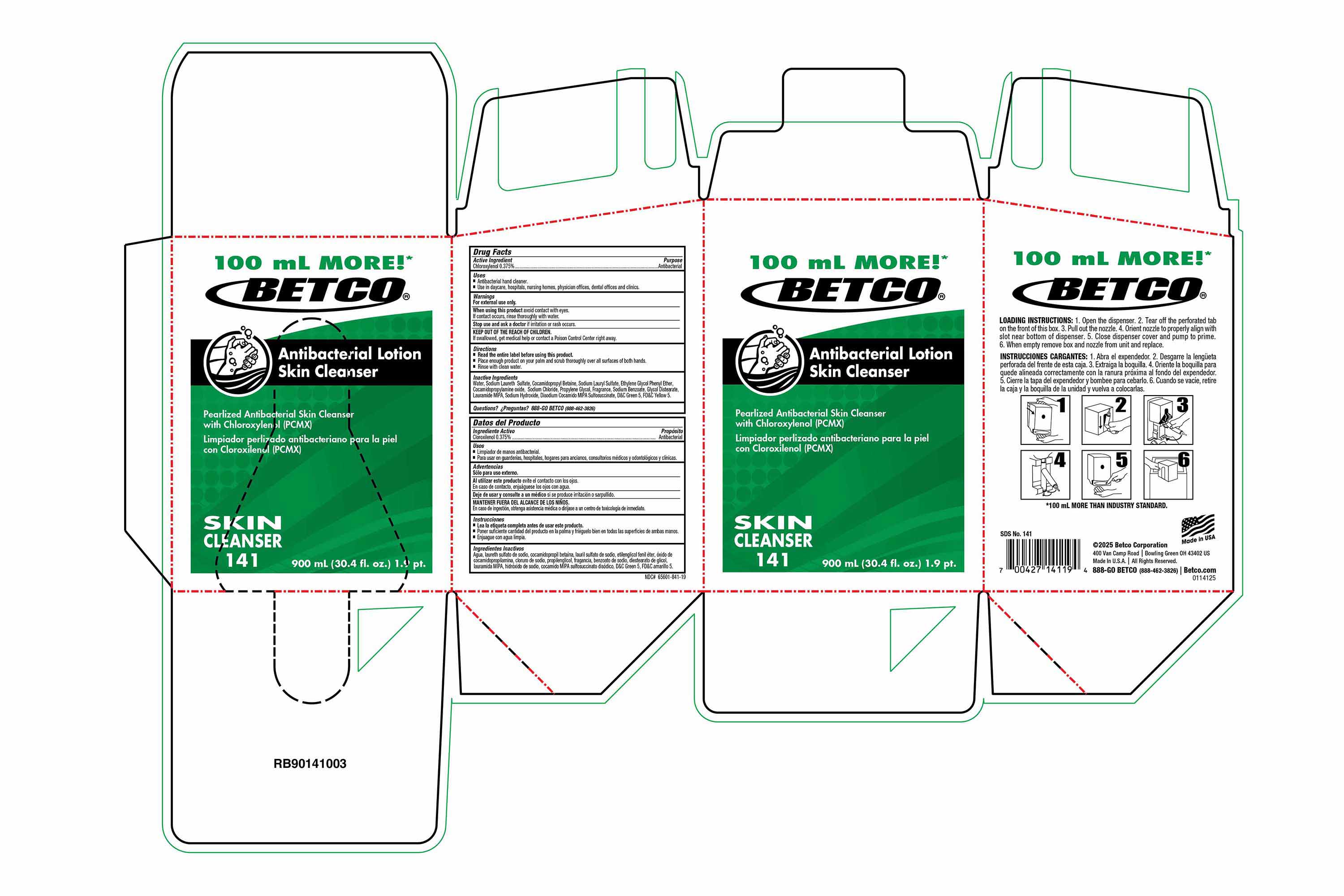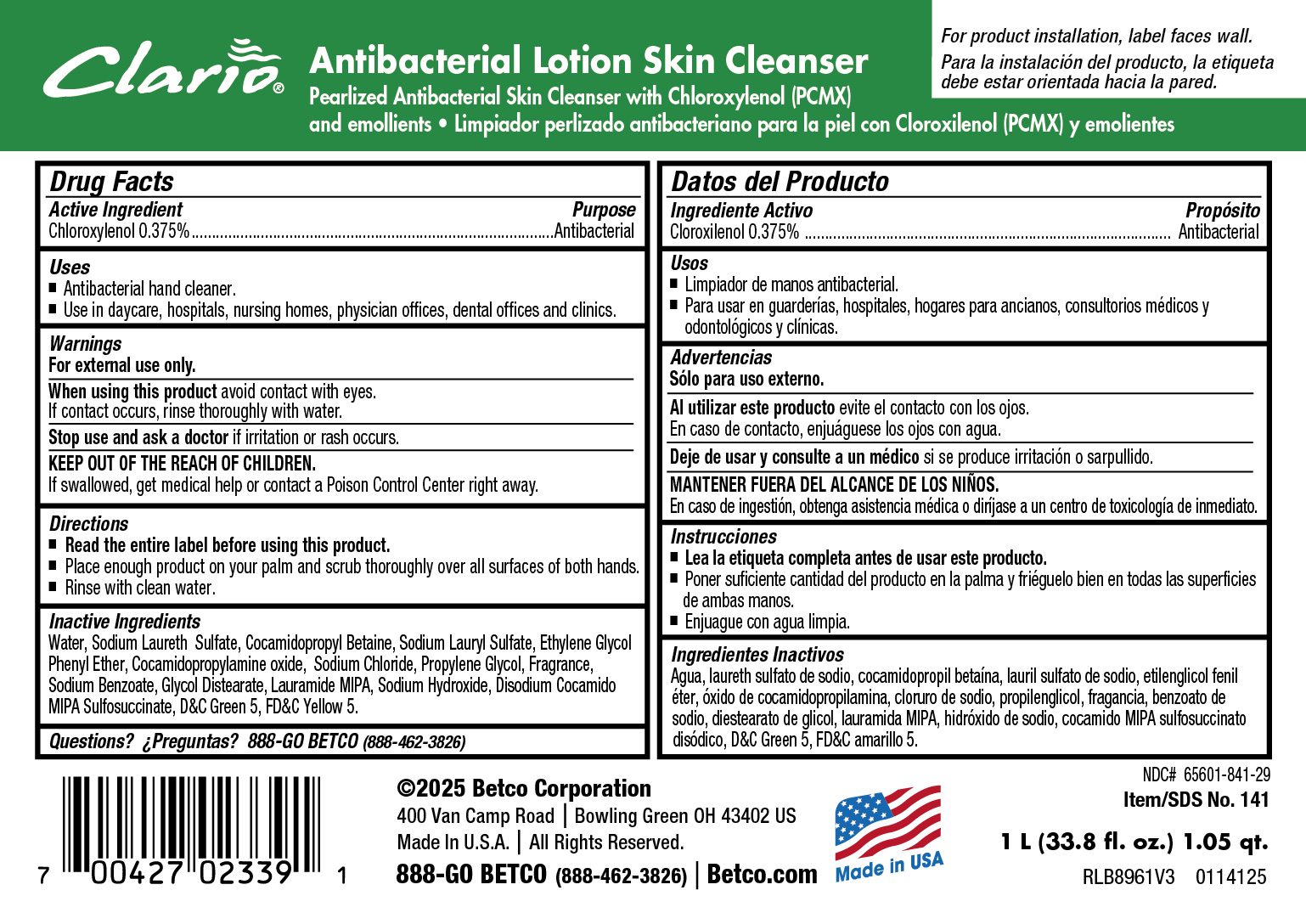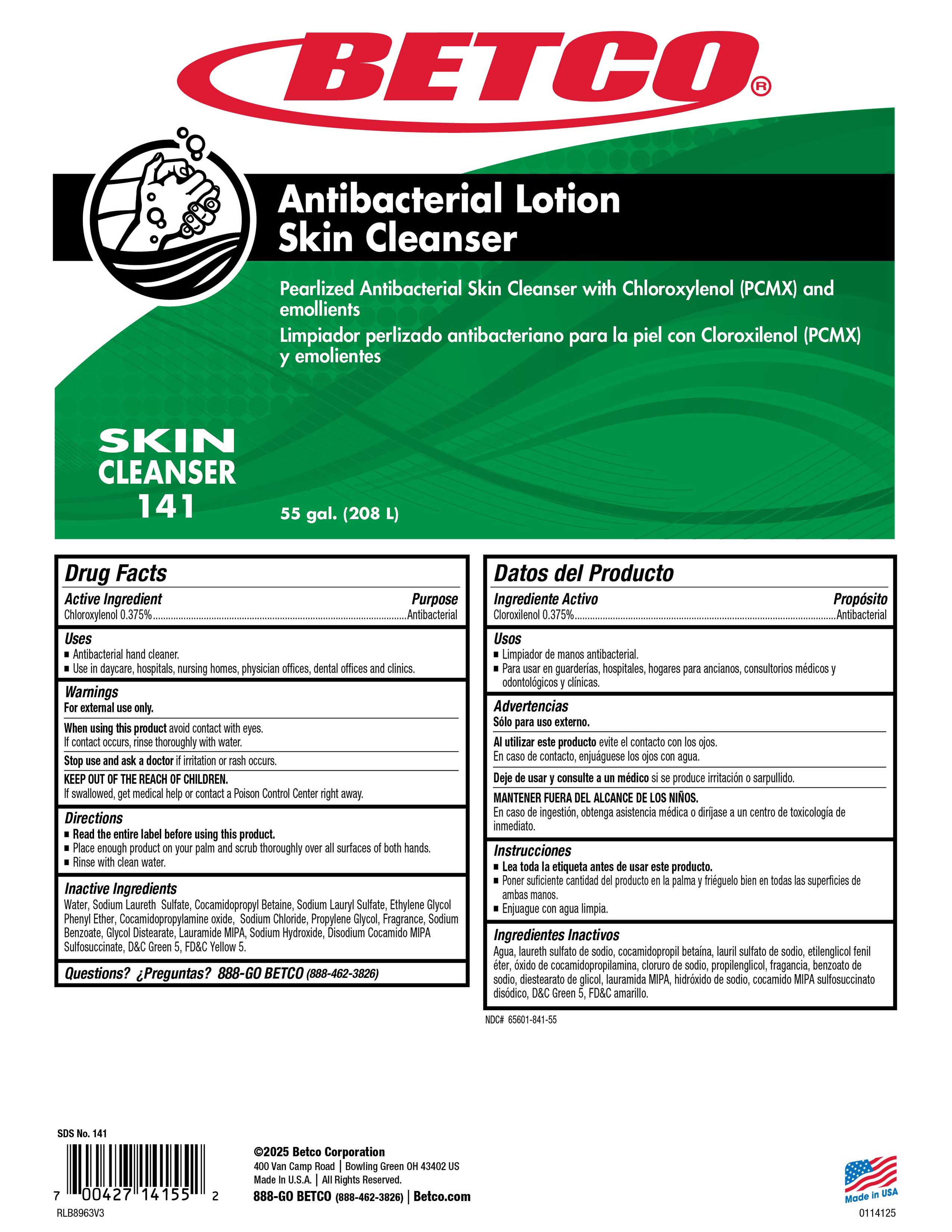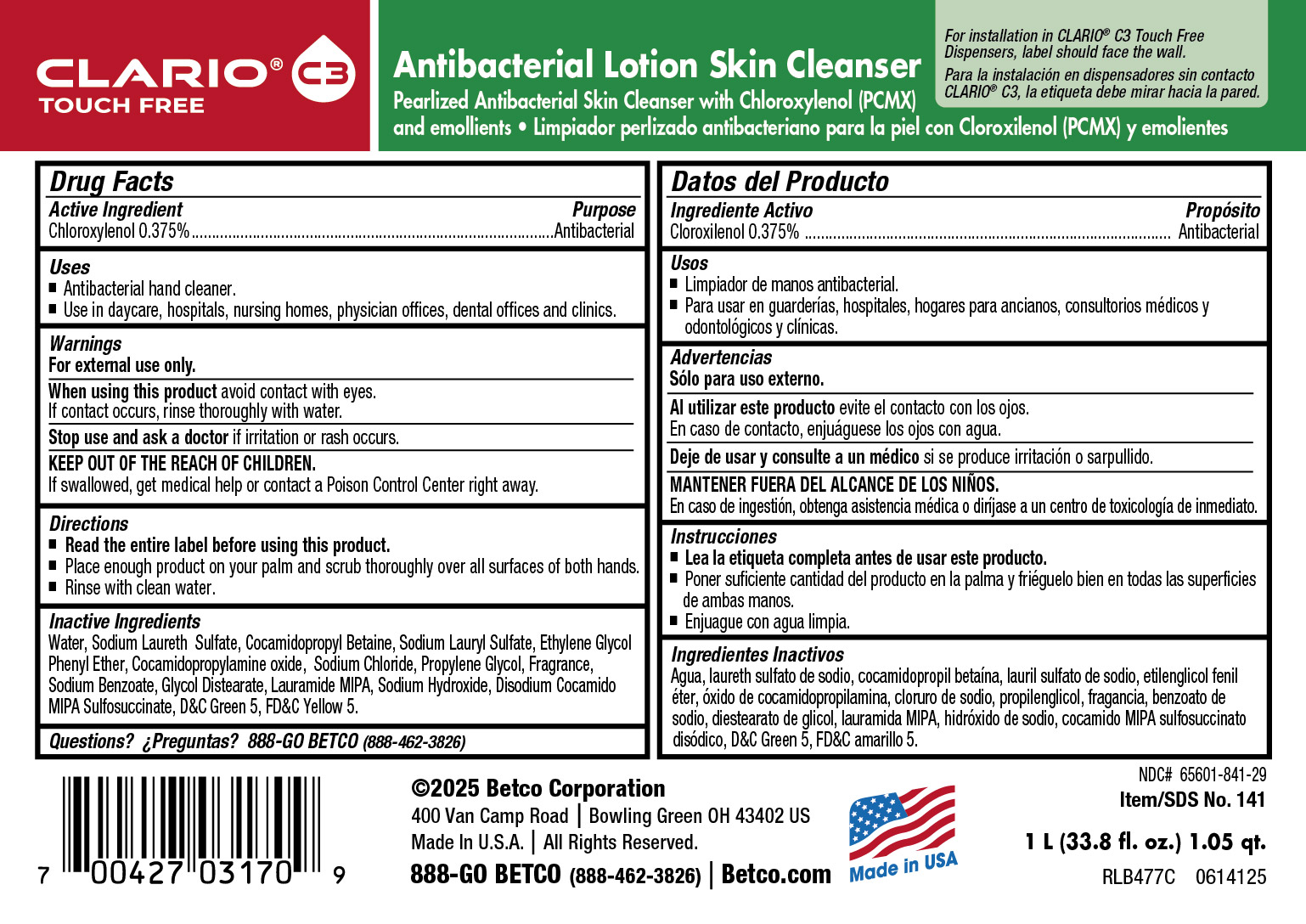 DRUG LABEL: Antibacterial Lotions Skin Cleanser
NDC: 65601-841 | Form: SOAP
Manufacturer: Betco Corporation, Ltd.
Category: otc | Type: HUMAN OTC DRUG LABEL
Date: 20250707

ACTIVE INGREDIENTS: CHLOROXYLENOL 4 mg/1 mL
INACTIVE INGREDIENTS: PHENYLETHYL ALCOHOL; ETHYLENE BRASSYLATE; 2-ISOBUTYL-4-METHYLTETRAHYDROPYRAN-4-OL; 2,6-DIMETHYL-5-HEPTENAL; VERDYL ACETATE; 1-(2,3,8,8-TETRAMETHYL-1,2,3,4,5,6,7,8-OCTAHYDRONAPHTHALEN-2-YL)ETHANONE; .ALPHA.-AMYLCINNAMALDEHYDE; .BETA.-CITRONELLOL, (+/-)-; 2-TERT-BUTYLCYCLOHEXYL ACETATE; 3-(3,4-METHYLENEDIOXYPHENYL)-2-METHYLPROPANAL; BENZYL SALICYLATE; COCAMIDOPROPYLAMINE OXIDE; .GAMMA.-UNDECALACTONE; 4-ACETOXY-3-PENTYLTETRAHYDROPYRAN; DIHYDROMYRCENOL; LAURIC ISOPROPANOLAMIDE; SODIUM CARBONATE; GLYCOL DISTEARATE; BENZYL ACETATE; SODIUM HYDROXIDE; HEXYL SALICYLATE; HEXAHYDRO-4,7-METHANOINDEN-6-YL PROPIONATE; CALCIUM SILICATE; SODIUM LAURYL SULFATE; .ALPHA.-HEXYLCINNAMALDEHYDE; ETHYLENE OXIDE; LINALOOL, (+/-)-; TRIBASIC CALCIUM PHOSPHATE; SODIUM ALUMINIUM SILICATE; WATER; SODIUM LAURETH SULFATE; COCAMIDOPROPYL BETAINE; PROPYLENE GLYCOL; SODIUM CHLORIDE; D&C GREEN NO. 5; FD&C YELLOW NO. 5; PHENOXYETHANOL; SODIUM BENZOATE

Antibacterial LotionSkin Cleanser

Active Ingredient

Chloroxylenol 0.40%

Uses

- Antibacterial hand cleaner.
- Use in daycare, hospitals, nursing homes, physicians offices, dental offices and clinics

Warnings

- For external use only.
- Avoid contact with eyes.
- Children under the age of 6 should be supervised by an adult when using this product.
- Discontinue use is irritation or redness develops.
- If irritation persists for more than 72 hours, consult a physician.
- KEEP OUT OF REACH OF CHILDREN.
- If swallowed, get medical help or contact a Poison Control Center right away.

Directions

- Read the entire label before using this product.
- Dispense 2 pumps of product onto palm of hand and scrub thoroughly over all surfaces of both hands.
- Rinse with clean water.

Inactive Ingredients

Water, Sodium Chloride, Sodium Laureth Sulfate, Cocamidopropyl Betaine, Sodium Lauryl Sulfate, Ethylene Glycol Phenyl Ether, Glycerin, Fragrance, Propylene Glycol, Sodium Hydroxide, Cocamidopropylamine Oxide, Sodium Benzoate, Glycol Distearate, Lauramide MIPA, Disodium Cocamido MIPA Sulfosuccinate, D&C Green 5, FD&C Yellow 5.

Purpose

Antibacterial

KEEP OUT OF REACH OF CHILDREN

Antibacterial Lotion Skin Cleanser

KEEP OUT OF REACH OF CHILDREN

©2017 Betco Corporation
400 Van Camp Road Bowling Green, Ohio 43402
Made In U.S.A. All Rights Reserved.

888-GO BETCO (888-462-3826) | Betco.com